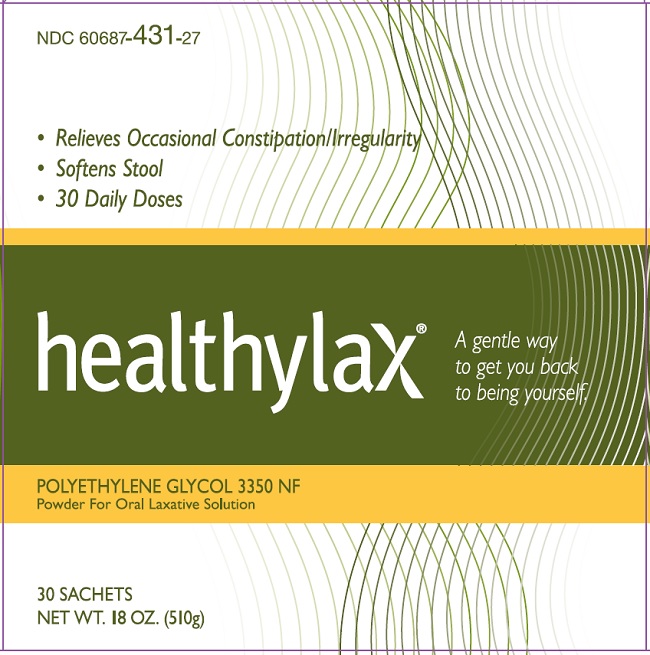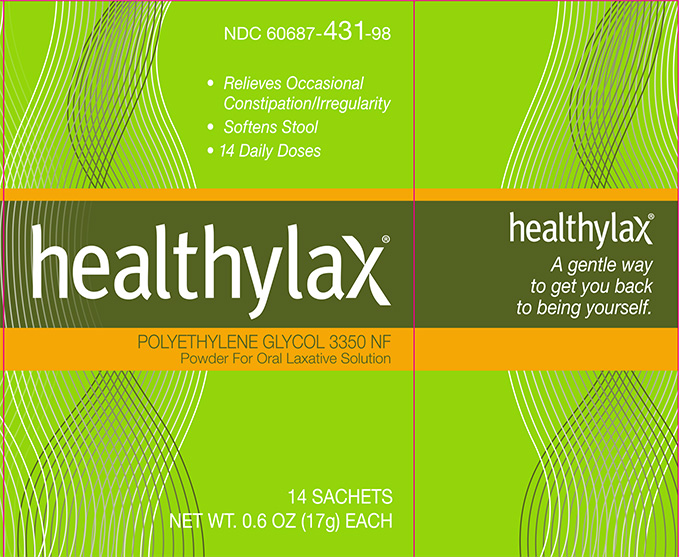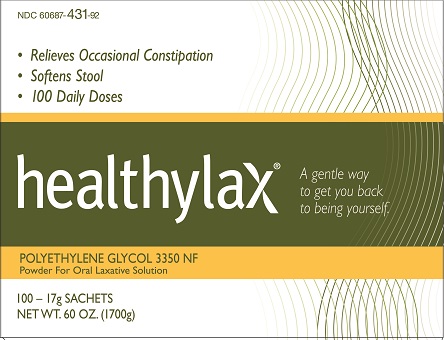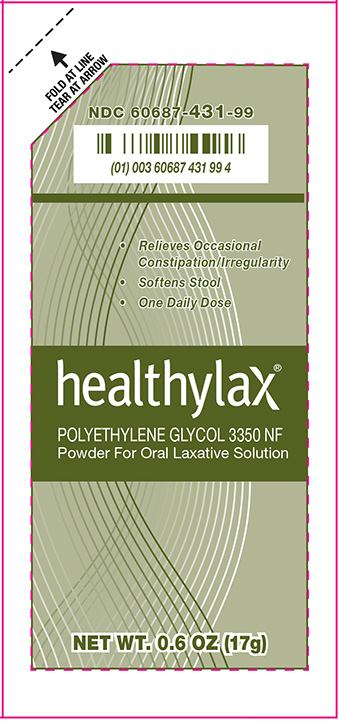 DRUG LABEL: Polyethylene Glycol 3350
NDC: 60687-431 | Form: POWDER, FOR SOLUTION
Manufacturer: American Health Packaging
Category: otc | Type: HUMAN OTC DRUG LABEL
Date: 20260218

ACTIVE INGREDIENTS: POLYETHYLENE GLYCOL 3350 17 g/17 g

Drug Facts
Polyethylene Glycol 3350, Powder for Oral Solution

Active Ingredient (in each sachet)

Polyethylene Glycol 3350, NF 17g

Purpose

Laxative

Uses

- relieves occasional constipation (irregularity)
- generally produces a bowel movement in 1 to 3 days

Warnings

Allergy alert: Do not use if you are allergic to polyethylene glycol.

Do not use if you have kidney disease, except under the advice and supervision of a doctor

Ask a doctor before use if you have

- nausea, vomiting or abdominal pain
- a sudden change in bowel habits that lasts over 2 weeks
- irritable bowel syndrome

Ask a doctor of pharmacist

before use if you are taking a prescription drug

When using this product

you may have loose, watery, more frequent stools

Stop use and ask a doctor if

- you have rectal bleeding or your nausea, bloating, cramping or abdominal pain gets worse. These may be signs of a serious condition.
- you get diarrhea
- you need to use a laxative for longer than 1 week

If pregnant or breast-feeding,

ask a health professional before use.

Keep out of the reach of children.

In case of overdose, get medical help or contact a Poison Control Center right away.

Directions

- do not take more than directed unless advised by your doctor
- adults and children 17 years of age and older:
- use once a day
- stir and dissolve one sachet of powder (17 g) in any 4 to 8 ounces of beverage (cold, hot or room temperature) then drink
- do not combine with starch-based thickeners used for difficulty swallowing.
- ensure that the powder is fully dissolved before drinking
- do not drink if there are any clumps
- do not use more than 7 days
- children 16 years of age or under: ask a doctor

Other Information

- store at 20° - 25°C (68° - 77°F)
- do not use if foil is open or broken.

Inactive Ingredients

none

Questions or comments?

1-800-707-4621 or www.americanhealthpackaging.com

© 2023 & Distributed by
American Health Packaging
Columbus, Ohio 43217 USA

All rights reserved.

1047662/1047664/1049041/1046550

Package/Label Display Panel - Carton - 17 g - 14UD

NDC 60687- 431-98

healthylax®
POLYETHYLENE GLYCOL 3350 NF
Powder for Oral Laxative Solution

14 SACHETS
Net Wt. 0.6 OZ (17g) EACH

Distributed by American Health Packaging, Columbus, Ohio 43217

PACKAGE/LABEL DISPLAY PANEL - CARTON - 17 G - 30UD

NDC 60687- 431-27

healthylax®
POLYETHYLENE GLYCOL 3350 NF
Powder for Oral Laxative Solution

30 SACHETS
Net Wt. 18 OZ (510g)

Distributed by American Health Packaging, Columbus, Ohio 43217

Package/Label Display Panel - Carton - 17 g - 100UD

NDC 60687- 431-92

healthylax®
P OLYETHYLENE GLYCOL 3350 NF
Powder for Oral Laxative Solution

100 - 17 g SACHETS
Net Wt. 0.6 OZ (1700g)

Distributed by American Health Packaging, Columbus, Ohio 43217

Package/Label Display Panel – Sachet – 17 g

NDC 60687- 431-99

healthylax®
POLYETHYLENE GLYCOL 3350 NF
Powder for Oral Laxative Solution

Net Wt. 0.6 OZ (17g)

Distributed by American Health Packaging, Columbus, Ohio 43217